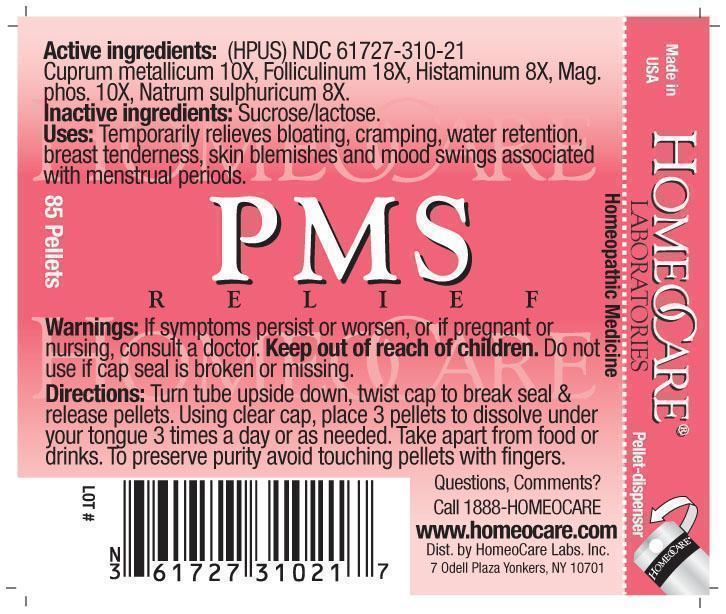 DRUG LABEL: PMS Relief
NDC: 61727-310 | Form: PELLET
Manufacturer: Homeocare Laboratories
Category: homeopathic | Type: HUMAN OTC DRUG LABEL
Date: 20181226

ACTIVE INGREDIENTS: COPPER 10 [hp_X]/4 g; ESTRONE 18 [hp_X]/4 g; HISTAMINE DIHYDROCHLORIDE 8 [hp_X]/4 g; MAGNESIUM PHOSPHATE, TRIBASIC, PENTAHYDRATE 10 [hp_X]/4 g; SODIUM SULFATE 8 [hp_X]/4 g
INACTIVE INGREDIENTS: SUCROSE; LACTOSE

PMS Relief

Active ingredients:

Cuprum metallicum 10X, Folliculinum 18X, Histaminum 8X, Mag. phos. 10X, Natrum sulphuricum 8X.

Inactive ingredients:

Sucrose/lactose.

Purpose:

Temporarily relieves bloating, cramping, water retention, breast tenderness, skin blemishes and mood swings associated with menstrual periods.

Indications & Usage:

Turn tube upside down, twist cap to break seal & release pellets. Using clear cap, place 3 pellets to dissolve under your tongue 3 times a day or as needed. Take apart from food or drinks. To preserve purity avoid touching pellets with fingers.

Keep out of reach of children.

Warnings:

If symptoms persist or worsen, or if pregnant or nursing, consult a doctor. Keep out of reach of children. Do not use if cap seal is broken or missing.

Dosage & Administration:

Turn tube upside down, twist cap to break seal & release pellets. Using clear cap, place 3 pellets to dissolve under your tongue 3 times a day or as needed. Take apart from food or drinks. To preserve purity avoid touching pellets with fingers.

PMS Relief

Homeopathic Medicine

85 Pellets

hcl label pms 2012.jpg